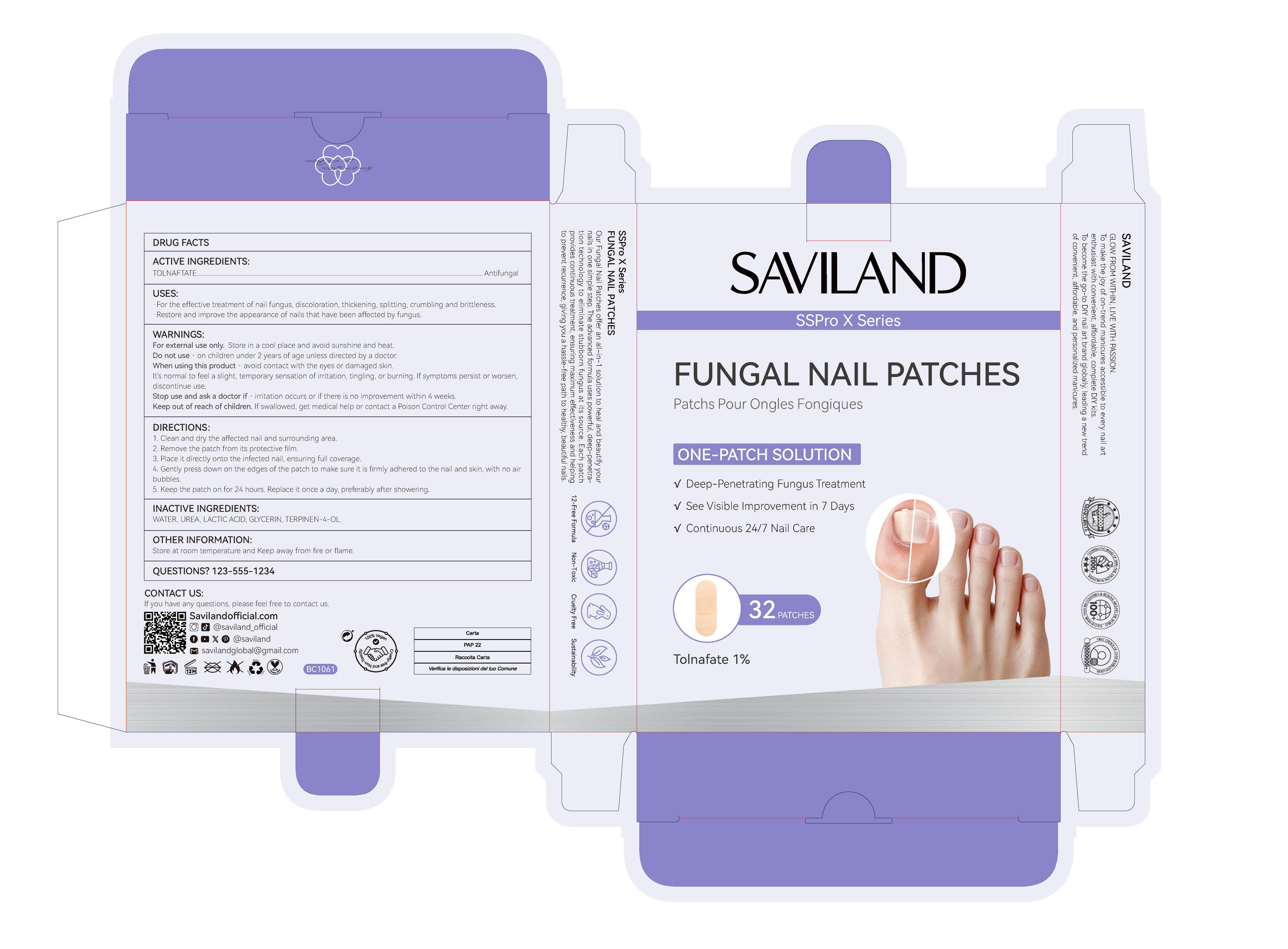 DRUG LABEL: Fungal Nail Patches
NDC: 85966-006 | Form: PATCH
Manufacturer: GUANGZHOU SAWEILAN IMPORT & EXPORT TRADING CO., LTD
Category: otc | Type: HUMAN OTC DRUG LABEL
Date: 20250928

ACTIVE INGREDIENTS: TOLNAFTATE 0.01 g/1 1
INACTIVE INGREDIENTS: GLYCERIN; 4-TERPINEOL; LACTIC ACID; UREA; WATER

85966-006 Fungal Nail Patches

ACTIVE INGREDIENT

TOLNAFTATE 1%

PURPOSE

Antifungal

INDICATIONS AND USAGE

For the effective treatment of nall fungus, discoloration, thickening, splitting, crumbling and brittleness.
Restore and improve the appearance of nails that have been affected by fungus.

WARNINGS

For external use only. Store in a cool place and avoid sunshine and heat.

Do not use · on children under 2 years of age unless directed by a doctor.

When using this product · avoid contact with the eyes or damaged skin.It's normal to feel a slight, temporary sensation of irritation, tingling, or burning. lf symptoms persist or worsen,discontinue use.

Stop use and ask a doctor if . irritation occurs or if there is no improvement within 4 weeks.

Keep out of reach of children. lf swallowed, get medical help or contact a Poison Control Center right away.

DOSAGE AND ADMINISTRATION

1.Clean and dry the affected nail and surrounding area.
2.Remove the patch from its protective film.
3.Place it directly onto the infected nail, ensuring full coverage.
4. Gently press down on the edges of the patch to make sure it is firmly adhered to the nail and skin, with no airbubbles.
5. Keep the patch on for 24 hours. Replace it once a day, preferably after showering.

INACTIVE INGREDIENT

WATER
UREA
LACTIC ACID
GLYCERIN
TERPINEN-4-OL